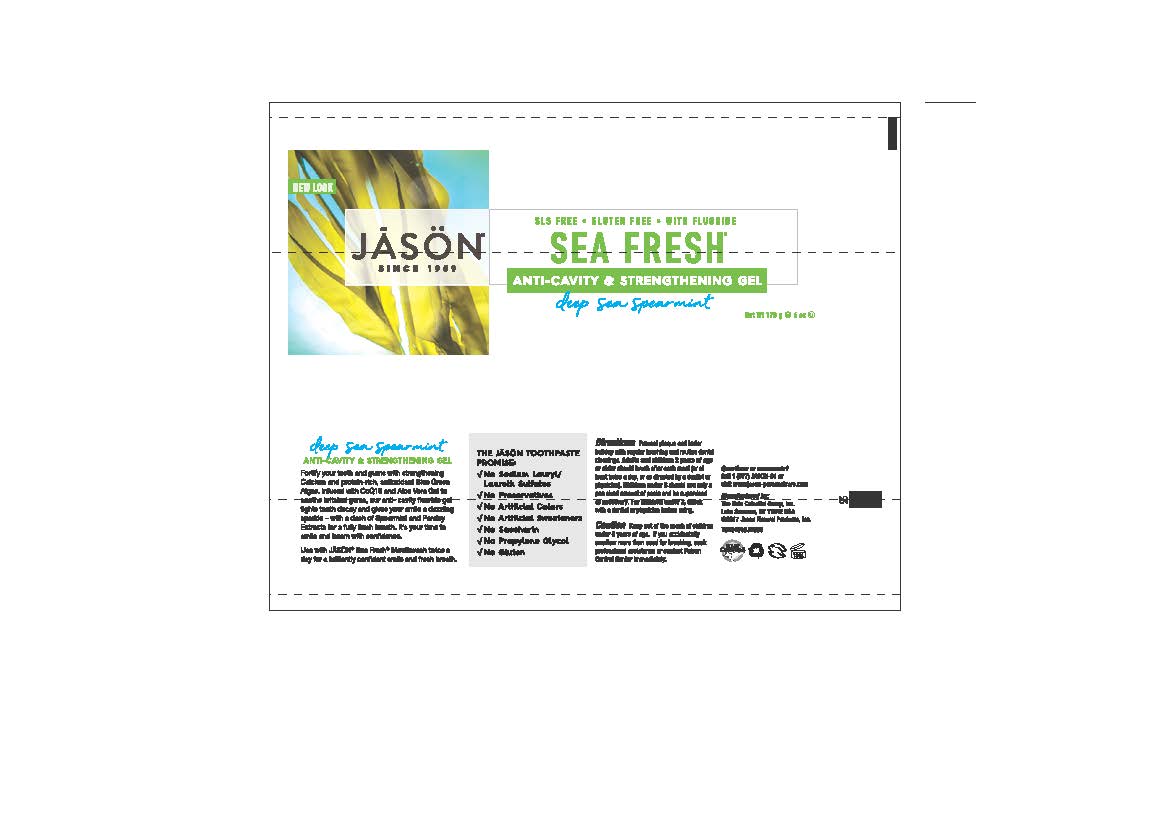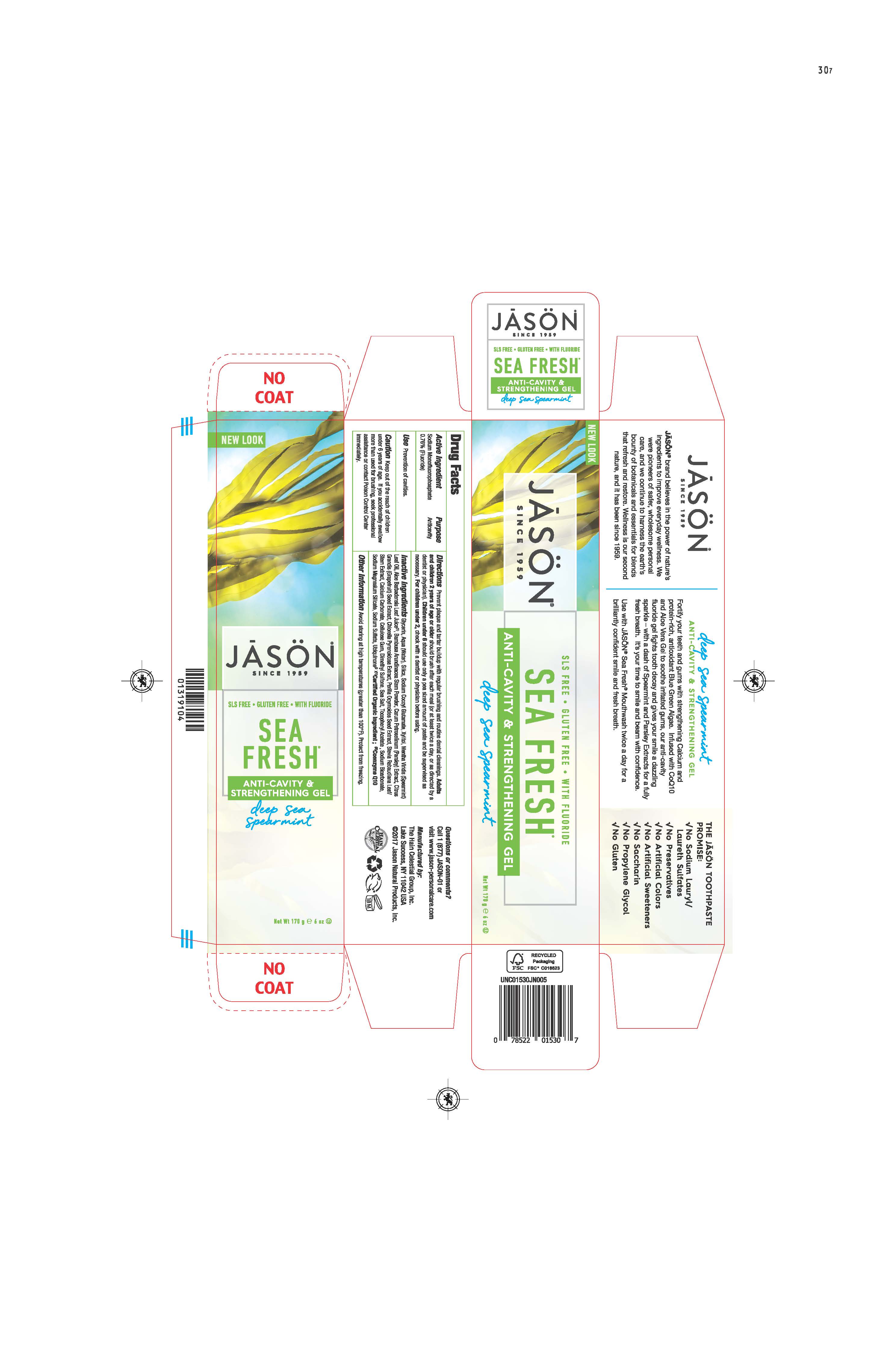 DRUG LABEL: Jason Sea Fresh Anticavity Deep Sea Spearmint
NDC: 61995-0530 | Form: GEL
Manufacturer: The Hain Celestial Group, Inc.
Category: otc | Type: HUMAN OTC DRUG LABEL
Date: 20210412

ACTIVE INGREDIENTS: SODIUM MONOFLUOROPHOSPHATE 0.76 g/100 g
INACTIVE INGREDIENTS: CHLORELLA PYRENOIDOSA; SODIUM SULFATE; SODIUM COCOYL GLUTAMATE; GLYCERIN; WATER; SILICON DIOXIDE; XYLITOL; ALOE VERA LEAF; BAMBUSA ARUNDINACEA STEM; CITRUS MAXIMA SEED; PARSLEY; PERILLA FRUTESCENS SEED; STEVIA REBAUDIUNA LEAF; SPEARMINT OIL; UBIDECARENONE; MAGNESIUM SILICATE; SEA SALT; CALCIUM CARBONATE; CARBOXYMETHYLCELLULOSE SODIUM; DIMETHYL SULFONE; SODIUM BICARBONATE; .ALPHA.-TOCOPHEROL ACETATE

Jason Sea Fresh Anticavity Deep Sea Spearmint

ACTIVE INGREDIENT

Sodium Monofluorophosphate 0.76%

PURPOSE

Anticavity

INDICATIONS AND USAGE

use: Prevention of cavities

WARNINGS

Avoid storing at high temperatures (greater than 100°F). Protect from freezing. If you accidentally swalow more than used for brushing, seek professional assistance or contact Poison Control immediately.

Keep out of reach of children under 6 years of age.If you accidentally swallow more than used for brushing, get medical help or contact Poison Control Center immediately.

DOSAGE AND ADMINISTRATION

Prevent plaque and tartarbuildup with regular drushing. Adults and children 2 years of age or older should brush teeth after each meal (or at least twice a day, or as directed by a dentist or physician). Children under 6: Should use only a pea sized amount of paste and be supervised as necessary. Children under 2, check with a dentist or physician before using.

INACTIVE INGREDIENT

Glycerin, Aqua (Water), Silica, Sodium Cocoyl Glutamate, Xylitol, Mentha Viridis (Spearmint) Leaf Oil, Aloe Barbadensis Leaf Juice (1),Aphanizomenon Flos-Aquae Powder, Bambusa Arundinacea Stem Powder, Carum Petroselinum (Parsley) Extract,Citrus Grandis (Grapefruit) Seed Extract, Perilla Ocymoides Seed Extract, Stevia Rebaudiana Leaf/Steam Extract, Calcium Carbonate, Cellulose Gum, Dimethyl Sulfone, Sea Salt, Tocopheryl Acetate, Sodium Bicarbonate, Sodium Magnesium Silicate, Sodium Sulfatre, Ubiquinone (2).

(1) Certified Organic Ingredients

(2) Coenzyme Q10